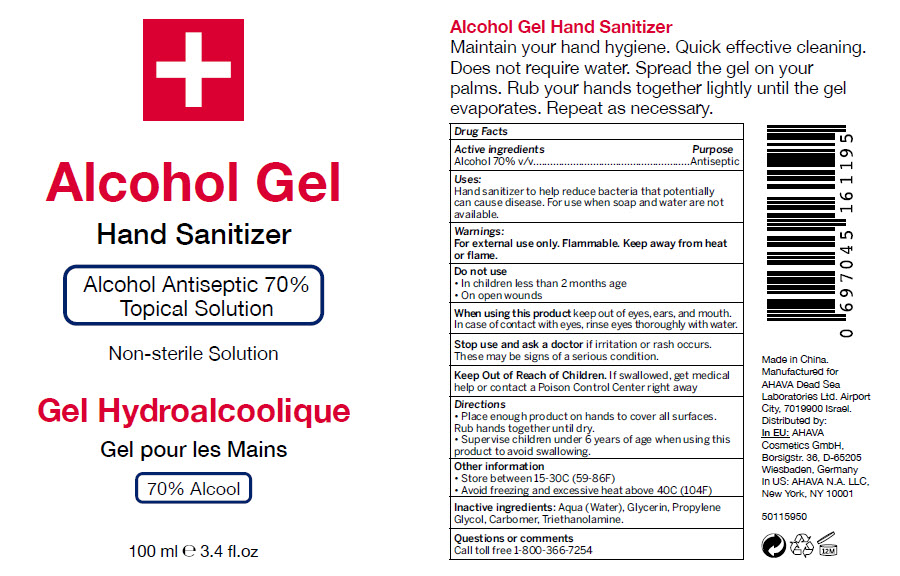 DRUG LABEL: Hand Sanitizer
NDC: 60289-289 | Form: GEL
Manufacturer: AHAVA Dead Sea Laboratories Ltd
Category: otc | Type: HUMAN OTC DRUG LABEL
Date: 20200430

ACTIVE INGREDIENTS: Alcohol 70 mL/100 mL
INACTIVE INGREDIENTS: Water; Glycerin; Propylene Glycol; Carbomer Homopolymer, Unspecified Type; TROLAMINE

Hand Sanitizer

Drug Facts

Active ingredients

Alcohol 70% v/v

Purpose

Antiseptic

Uses

Hand sanitizer to help reduce bacteria that potentially can cause disease. For use when soap and water are not available.

Warnings

For external use only. Flammable. Keep away from heat or flame.

Do not use

- In children less than 2 months age
- On open wounds

When using this product keep out of eyes, ears, and mouth. In case of contact with eyes, rinse eyes thoroughly with water.

Stop use and ask a doctor if irritation or rash occurs. These may be signs of a serious condition.

Keep Out of Reach of Children. If swallowed, get medical help or contact a Poison Control Center right away

Directions

- Place enough product on hands to cover all surfaces. Rub hands together until dry.
- Supervise children under 6 years of age when using this product to avoid swallowing.

Other information

- Store between 15-30C (59-86F)
- Avoid freezing and excessive heat above 40C (104F)

Inactive ingredients

Aqua (Water), Glycerin, Propylene Glycol, Carbomer, Triethanolamine.

Questions or comments

Call toll free 1-800-366-7254

Distributed by:
In US: AHAVA N.A. LLC,
New York, NY 10001

PRINCIPAL DISPLAY PANEL - 100 ml Bottle Label

Alcohol Gel

Hand Sanitizer

Alcohol Antiseptic 70%
Topical Solution

Non-sterile Solution

100 ml ℮ 3.4 fl.oz